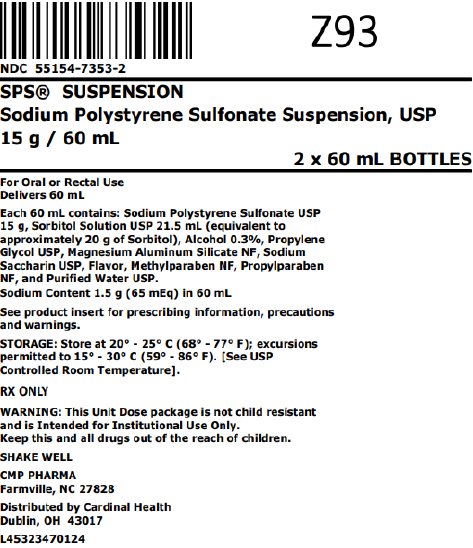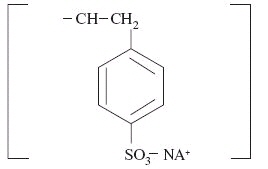 DRUG LABEL: Sodium Polystyrene Sulfonate
NDC: 55154-7353 | Form: SUSPENSION
Manufacturer: Cardinal Health 107, LLC
Category: prescription | Type: HUMAN PRESCRIPTION DRUG LABEL
Date: 20251029

ACTIVE INGREDIENTS: SODIUM POLYSTYRENE SULFONATE 15 g/60 mL
INACTIVE INGREDIENTS: SORBITOL 21.5 mL/60 mL; ALCOHOL 0.18 mL/60 mL; WATER; PROPYLENE GLYCOL; MAGNESIUM ALUMINUM SILICATE; SACCHARIN SODIUM; METHYLPARABEN; PROPYLPARABEN

SPS® SUSPENSION
Sodium Polystyrene
Sulfonate Suspension, USP

CMP Pharma, Inc.
Cation-Exchange Resin
Rx Only

DESCRIPTION

Sodium Polystyrene Sulfonate Suspension USP (SPS® Suspension) can be administered orally or in an enema. It is a cherry-flavored suspension containing 15 grams of cation-exchange resin (Sodium Polystyrene Sulfonate USP); 21.5 mL of Sorbitol Solution USP (equivalent to approximately 20 grams of Sorbitol); 0.18 mL (0.3%) of Alcohol per 60 mL of suspension. Also contains Purified Water USP; Propylene Glycol USP; Magnesium Aluminum Silicate NF; Sodium Saccharin USP; Methylparaben NF; Propylparaben NF; and flavor.

Sodium polystyrene sulfonate is a benzene, diethenyl-, polymer with ethenylbenzene, sulfonated, sodium salt and has the following structural formula:

The sodium content of the suspension is 1500 mg (65 mEq) per 60 mL. It is a brown, slightly viscous suspension with an in‑vitro exchange capacity of approximately 3.1 mEq (in-vivo approximately 1 mEq) of potassium per 4 mL (1 gram) of suspension. It can be administered orally or in an enema.

CLINICAL PHARMACOLOGY

As the resin passes along the intestine or is retained in the colon after administration by enema, the sodium ions are partially released and are replaced by potassium ions. For the most part, this action occurs in the large intestine, which excretes potassium ions to a greater degree than does the small intestine. The efficiency of this process is limited and unpredictably variable. It commonly approximates the order of 33%, but the range is so large that definitive indices of electrolyte balance must be clearly monitored.

Metabolic data are unavailable.

INDICATION AND USAGE

SPS® Suspension is indicated for the treatment of hyperkalemia.

CONTRAINDICATIONS

SPS® Suspension is contraindicated in the following conditions: patients with hypokalemia, patients with a history of hypersensitivity to polystyrene sulfonate resins, obstructive bowel disease, oral or rectal administration in neonates (See PRECAUTIONS).

WARNINGS

Intestinal Necrosis

Cases of intestinal necrosis, which may be fatal, and other serious gastrointestinal adverse events (bleeding, ischemic colitis, perforation) have been reported in association with sodium polystyrene sulfonate use. The majority of these cases reported the concomitant use of sorbitol. Risk factors for gastrointestinal adverse events were present in many of the cases including prematurity, history of intestinal disease or surgery, hypovolemia, and renal insufficiency and failure. Concomitant administration of additional sorbitol is not recommended (see PRECAUTIONS, Drug Interactions).

- Use only in patients who have normal bowel function. Avoid use in patients who have not had a bowel movement post-surgery.
- Avoid use in patients who are at risk for developing constipation or impaction (including those with history of impaction, chronic constipation, inflammatory bowel disease, ischemic colitis, vascular intestinal atherosclerosis, previous bowel resection, or bowel obstruction).
- Discontinue use in patients who develop constipation.

Alternative Therapy in Severe Hyperkalemia

Since the effective lowering of serum potassium with sodium polystyrene sulfonate may take hours to days, treatment with this drug alone may be insufficient to rapidly correct severe hyperkalemia associated with states of rapid tissue breakdown (e.g., burns and renal failure) or hyperkalemia so marked as to constitute a medical emergency. Therefore, other definitive measures, including dialysis, should always be considered and may be imperative.

Hypokalemia

Serious potassium deficiency can occur from sodium polystyrene sulfonate therapy. The effect must be carefully controlled by frequent serum potassium determinations within each 24 hour period. Since intracellular potassium deficiency is not always reflected by serum potassium levels, the level at which treatment with sodium polystyrene sulfonate should be discontinued must be determined individually for each patient. Important aids in making this determination are the patient's clinical condition and electrocardiogram. Early clinical signs of severe hypokalemia include a pattern of irritable confusion and delayed thought processes.

Electrocardiographically, severe hypokalemia is often associated with a lengthened Q-T interval, widening, flattening, or inversion of the T wave, and prominent U waves. Also, cardiac arrhythmias may occur, such as premature atrial, nodal, and ventricular contractions, and supraventricular and ventricular tachycardias. The toxic effects of digitalis are likely to be exaggerated. Marked hypokalemia can also be manifested by severe muscle weakness, at times extending into frank paralysis.

Electrolyte Disturbances

Like all cation-exchange resins, sodium polystyrene sulfonate is not totally selective (for potassium) in its actions, and small amounts of other cations such as magnesium and calcium can also be lost during treatment. Accordingly, patients receiving sodium polystyrene sulfonate should be monitored for all applicable electrolyte disturbances.

Systemic Alkalosis

Systemic alkalosis has been reported after cation-exchange resins were administered orally in combination with nonabsorbable cation-donating antacids and laxatives such as magnesium hydroxide and aluminum carbonate. Magnesium hydroxide should not be administered with sodium polystyrene sulfonate. One case of grand mal seizure has been reported in a patient with chronic hypocalcemia of renal failure who was given sodium polystyrene sulfonate with magnesium hydroxide as a laxative (See PRECAUTIONS, Drug Interactions).

Risk of Aspiration

Cases of acute bronchitis or bronchopneumonia caused by inhalation of sodium polystyrene sulfonate particles has been reported. Patients with impaired gag reflex, altered level of consciousness, or patients prone to regurgitation may be at increased risk. Administer sodium polystyrene sulfonate suspension with the patient in an upright position.

Binding to Other Orally Administered Medications

Sodium polystyrene sulfonate suspension may bind orally administered medications, which could decrease their gastrointestinal absorption and lead to reduced efficacy. Administer other oral medications at least 3 hours before or 3 hours after sodium polystyrene sulfonate suspension. Patients with gastroparesis may require a 6 hour separation (see DOSAGE AND ADMINISTRATION and PRECAUTIONS, Drug Interactions).

PRECAUTIONS

Caution is advised when sodium polystyrene sulfonate is administered to patients who cannot tolerate even a small increase in sodium loads (i.e., severe congestive heart failure, severe hypertension, or marked edema). In such instances compensatory restriction of sodium intake from other sources may be indicated.

Precautions should be taken to ensure the use of adequate volumes of sodium-free cleansing enemas after rectal administration.

In the event of clinically significant constipation, treatment with SPS® Suspension should be discontinued until normal bowel motion is resumed (See WARNINGS, Intestinal Necrosis).

Drug Interactions

General Interactions

No formal drug interaction studies have been conducted in humans.
Sodium polystyrene sulfonate suspension has the potential to bind other drugs. In in-vitro binding studies, sodium polystyrene sulfonate was shown to significantly bind the oral medications (n=6) that were tested. Decreased absorption of lithium and thyroxine have also been reported with co-administration of sodium polystyrene sulfonate. Binding of sodium polystyrene sulfonate suspension to other oral medications could cause decreased gastrointestinal absorption and loss of efficacy when taken close to the time sodium polystyrene sulfonate suspension is administered. Administer sodium polystyrene sulfonate suspension at least 3 hours before or 3 hours after other oral medications. Patients with gastroparesis may require a 6 hour separation. Monitor for clinical response and/or blood levels where possible.

Antacids

The simultaneous oral administration of sodium polystyrene sulfonate with nonabsorbable cation-donating antacids and laxatives may reduce the resin's potassium exchange capability.

Nonabsorbable cation-donating antacids and laxatives

Systemic alkalosis has been reported after cation exchange resins were administered orally in combination with nonabsorbable cation-donating antacids and laxatives such as magnesium hydroxide and aluminum carbonate. Magnesium hydroxide should not be administered with sodium polystyrene sulfonate. One case of grand mal seizure has been reported in a patient with chronic hypocalcemia of renal failure who was given sodium polystyrene sulfonate with magnesium hydroxide as a laxative.

Intestinal obstruction due to concretions of aluminum hydroxide when used in combination with sodium polystyrene sulfonate has been reported.

Digitalis

The toxic effects of digitalis on the heart, especially various ventricular arrhythmias and A-V nodal dissociation, are likely to be exaggerated by hypokalemia, even in the face of serum digoxin concentrations in the "normal range" (See WARNINGS).

Sorbitol

Concomitant use of sorbitol with sodium polystyrene sulfonate has been implicated in cases of intestinal necrosis, which may be fatal (See WARNINGS).

Lithium

SPS® Suspension may decrease absorption of lithium.

Thyroxine

SPS® Suspension may decrease absorption of thyroxine.

Carcinogenesis, Mutagenesis, Impairment of Fertility

Studies have not been performed.

Pregnancy Category C

Animal reproduction studies have not been conducted with sodium polystyrene sulfonate. It is also not known whether sodium polystyrene sulfonate can cause fetal harm when administered to a pregnant woman or can affect reproduction capacity. Sodium polystyrene sulfonate should be given to a pregnant woman only if clearly needed.

Nursing Mothers

It is not known whether this drug is excreted in human milk. Because many drugs are excreted in human milk, caution should be exercised when sodium polystyrene sulfonate is administered to a nursing woman.

Pediatric Use

The effectiveness of SPS® Suspension in pediatric patients has not been established. The use of SPS® Suspension is contraindicated in neonates and especially in premature infants. In children and neonates, particular care should be observed with rectal administration, as excessive dosage could result in impaction of the resin. Precautions should be taken to ensure the use of adequate volumes of sodium-free cleansing enemas after rectal administration.

ADVERSE REACTIONS

SPS® Suspension may cause some degree of gastric irritation. Anorexia, nausea, vomiting, and constipation may occur especially if high doses are given. Also, hypokalemia, hypocalcemia, hypomagnesemia and significant sodium retention, and their related clinical manifestations, may occur (See WARNINGS). Occasionally diarrhea develops. Large doses in elderly individuals may cause fecal impaction (See PRECAUTIONS). Rare instances of intestinal necrosis have been reported. Intestinal obstruction due to concretions of aluminum hydroxide, when used in combination with sodium polystyrene sulfonate, has been reported.

The following events have been reported from worldwide post marketing experience:

- Fecal impaction following rectal administration, particularly in children;
- Gastrointestinal concretions (bezoars) following oral administration;
- Ischemic colitis, gastrointestinal tract ulceration or necrosis which could lead to intestinal perforation; and
- Rare cases of acute bronchitis and/or bronchopneumonia associated with inhalation of particles of polystyrene sulfonate (see WARNINGS).

To report suspected adverse reactions, contact CMP Pharma, Inc., toll free at 1-844-321-1443 or the FDA at 1-800-FDA-1088 or www.fda.gov/medwatch.

OVERDOSAGE

Overdosage may result in electrolyte disturbances including hypokalemia, hypocalcemia, and hypomagnesemia. Biochemical disturbances resulting from overdosage may give rise to clinical signs and symptoms of hypokalemia, including: irritability, confusion, delayed thought processes, muscle weakness, hyporeflexia, which may progress to frank paralysis and/or apnea. Tetany may occur. Electrocardiographic changes may be consistent with hypokalemia or hypocalcemia; cardiac arrhythmias may occur. Appropriate measures should be taken to correct serum electrolytes (potassium, calcium, magnesium), and the resin should be removed from the alimentary tract by appropriate use of laxatives or enemas.

DOSAGE AND ADMINISTRATION

Administer sodium polystyrene sulfonate suspension at least 3 hours before or 3 hours after other oral medications. Patients with gastroparesis may require a 6 hour separation (see WARNINGS and PRECAUTIONS, Drug Interactions).

The average daily adult dose is 15 g (60 mL) to 60 g (240 mL) of suspension. This is best provided by administering 15 g (60 mL) of SPS® Suspension one to four times daily. Each 60 mL of SPS® Suspension contains 1500 mg (65 mEq) of sodium. Since the in-vivo efficiency of sodium-potassium exchange resins is approximately 33%, about one-third of the resin's actual sodium content is being delivered to the body.

In smaller children and infants, lower doses should be employed by using as a guide a rate of 1 mEq of potassium per gram of resin as the basis for calculation. Administer with patient in an upright position (see WARNINGS).

SPS® Suspension may be introduced into the stomach through a plastic tube and, if desired, given with a diet appropriate for a patient in renal failure.

SPS® Suspension may also be given, although with less effective results, as an enema consisting (for adults) of 30 g (120 mL) to 50 g (200 mL) every six hours. The enema should be retained as long as possible and followed by a cleansing enema.

After an initial cleansing enema, a soft, large size (French 28) rubber tube is inserted into the rectum for a distance of about 20 cm, with the tip well into the sigmoid colon, and taped into place. The suspension is introduced at body temperature by gravity. The suspension is flushed with 50 or 100 mL of fluid, following which the tube is clamped and left in place. If back leakage occurs, the hips are elevated on pillows or a knee-chest position is taken temporarily. The suspension is kept in the sigmoid colon for several hours, if possible. Then the colon is irrigated with a sodium-free cleansing enema at body temperature in order to remove the resin. Two quarts of flushing solution may be necessary. The returns are drained constantly through a Y tube connection. Particular attention should be paid to this cleansing enema, because sorbitol is present in the vehicle.

The intensity and duration of therapy depend upon the severity and resistance of hyperkalemia.

SPS® Suspension should not be heated for to do so may alter the exchange properties of the resin.

HOW SUPPLIED

SPS® Suspension is a light brown, cherry-flavored suspension supplied in

Overbagged with 2 x 60 mL unit dose bottles in each bag, NDC 55154-7353-2

WARNING: This Unit Dose package is not child resistant and is Intended for Institutional Use Only. Keep this and all drugs out of the reach of children.

Dispense in a tight container, as defined in the USP. If repackaging into other containers, store in refrigerator and use within 14 days of packaging.

SHAKE WELL BEFORE USING.

Store at 20°-25°C (68°-77°F); excursions permitted to 15°-30°C (59°-86°F). [See USP Controlled Room Temperature].

CMP Pharma, Inc.
P.O. Box 147
Farmville, North Carolina 27828

Distributed By:

Cardinal Health

Dublin, OH 43017

L45323470124

Revised August 2021

3081 R0821

Package/Label Display Panel

NDC 55154-7353-2

SPS® SUSPENSION

Sodium Polystyrene Sulfonate Suspension, USP

15 g / 60 mL

2 x 60 mL BOTTLES